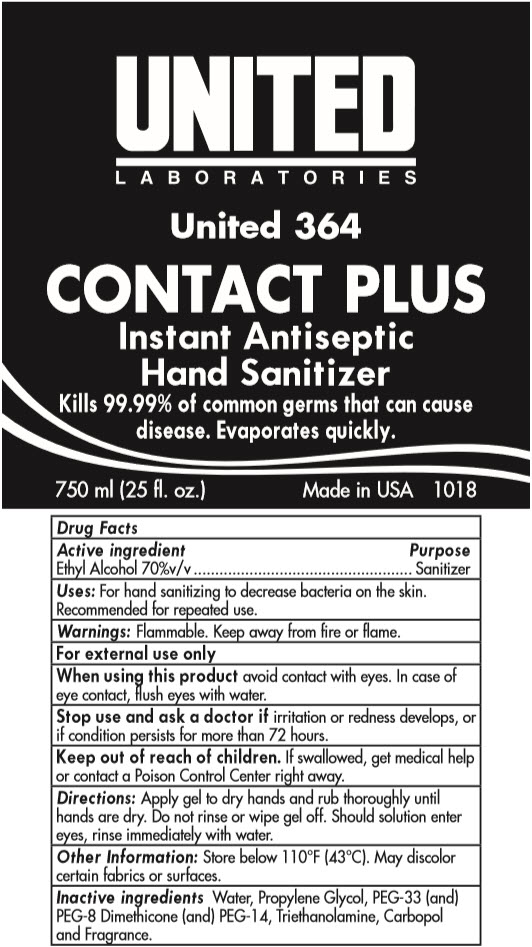 DRUG LABEL: Instant Antiseptic Hand Sanitizer
NDC: 63998-364 | Form: SOLUTION
Manufacturer: United Laboratories Inc.
Category: otc | Type: HUMAN OTC DRUG LABEL
Date: 20241125

ACTIVE INGREDIENTS: ALCOHOL 70 mL/100 mL
INACTIVE INGREDIENTS: WATER; PROPYLENE GLYCOL; POLYETHYLENE GLYCOL 1600; PEG-8 DIMETHICONE; POLYETHYLENE GLYCOL 700; TROLAMINE; CARBOMER HOMOPOLYMER, UNSPECIFIED TYPE

Instant Antiseptic Hand Sanitizer 63998-364

Drug Facts

Active ingredient

Ethyl Alcohol 70%v/v

Purpose

Sanitizer

Uses

For hand sanitizing to decrease bacteria on the skin. Recommended for repeated use.

Warnings

Flammable. Keep away from fire or flame.

For external use only

WHEN USING

When using this productavoid contact with eyes. In case of eye contact, flush eyes with water.

Stop use and ask a doctor ifirritation or redness develops, or if condition persists for more than 72 hours.

Keep out of reach of children.If swallowed, get medical help or contact a Poison Control Center right away.

Directions

Apply gel to dry hands and rub thoroughly until hands are dry. Do not rinse or wipe gel off. Should solution enter eyes, rinse immediately with water.

Other Information

Store below 110°F (43°C). May discolor certain fabrics or surfaces.

Inactive ingredients

Water, Propylene Glycol, PEG-33 (and) PEG-8 Dimethicone (and) PEG-14, Triethanolamine, Carbopol and Fragrance.

PRINCIPAL DISPLAY PANEL - 750 ml Bottle Label

UNITED
LABORATORIES

United 364

CONTACT PLUS

Instant Antiseptic
Hand Sanitizer

Kills 99.99% of common germs that can cause
disease. Evaporates quickly.

750 ml (25 fl. oz.)

Made in USA 1018